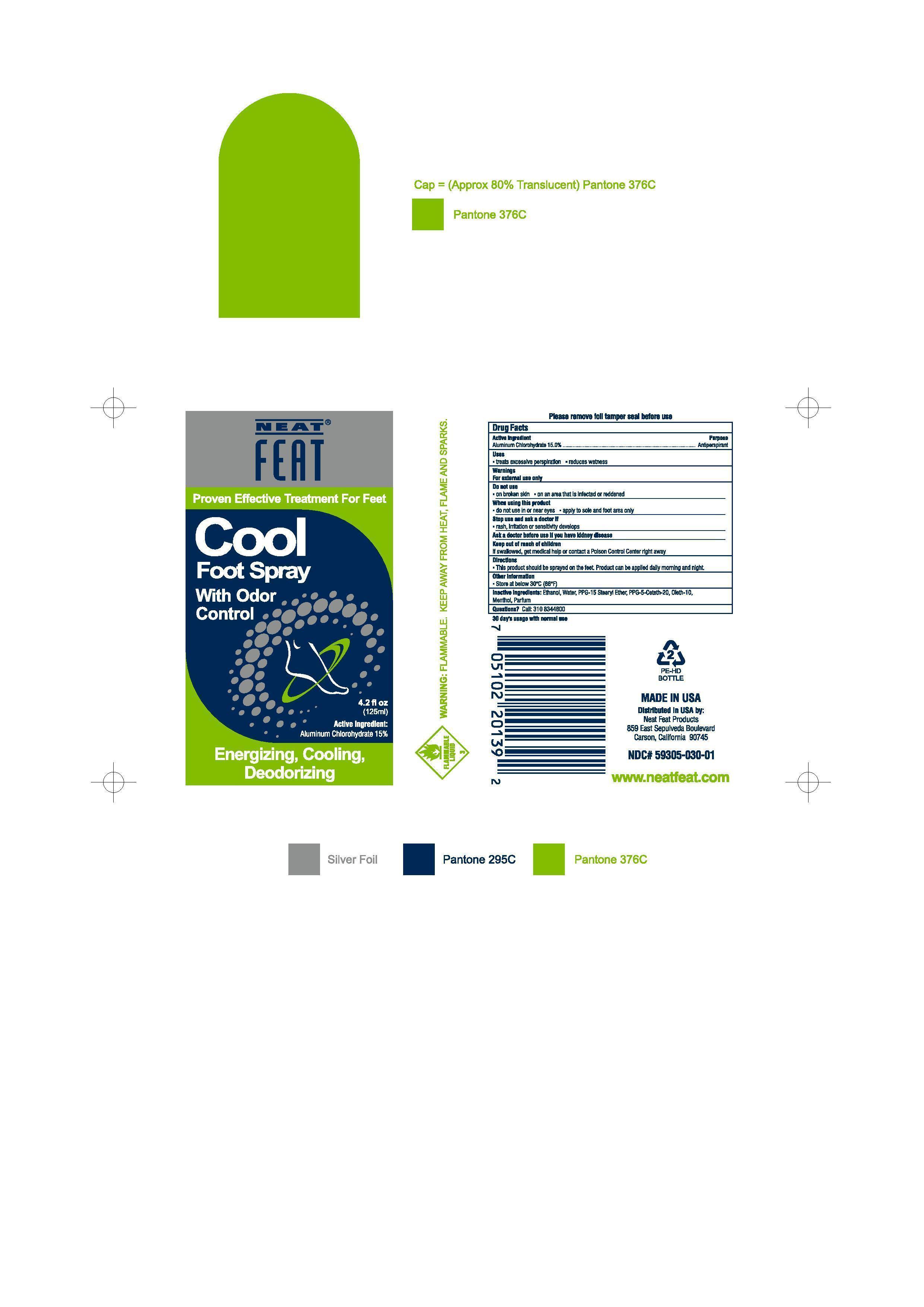 DRUG LABEL: Cool Foot
NDC: 59305-030 | Form: SPRAY
Manufacturer: NEAT FEAT PRODUCTS
Category: otc | Type: HUMAN OTC DRUG LABEL
Date: 20130903

ACTIVE INGREDIENTS: ALUMINUM CHLOROHYDRATE 12 g/125 g
INACTIVE INGREDIENTS: ACETALDEHYDE; water; PPG-15 STEARYL ETHER; PPG-5-CETETH-20; OLETH-10; MENTHOL

Active Ingredients

Aluminum Chlorohydrate 15.0%

Uses

Treats excessive perspiration

Reduses wetness

Keep out of reach of children

If swallowed, get medical help or contact Poison Control Center right away

INDICATIONS AND USAGE

Foot Spray With Odor Control

Warnings For external use only

Do not use On broken skin On an area that is infected or reddened

When using this product Do not use in or near eyes apply to sole and foot area only

Stop use an ask a doctor if rash, irritation or sensitivity develops

Ask a doctor before use if you have kidney disease

Directions

This product should be sprayed on the feet, Product can be applied daily morning and night

INACTIVE INGREDIENT

Inactive Ingredients: Ethanol, Water, PPG-15 Stearyl Ether, PPG-5-Ceteth-20, Oleth-10, Menthol, Parfum